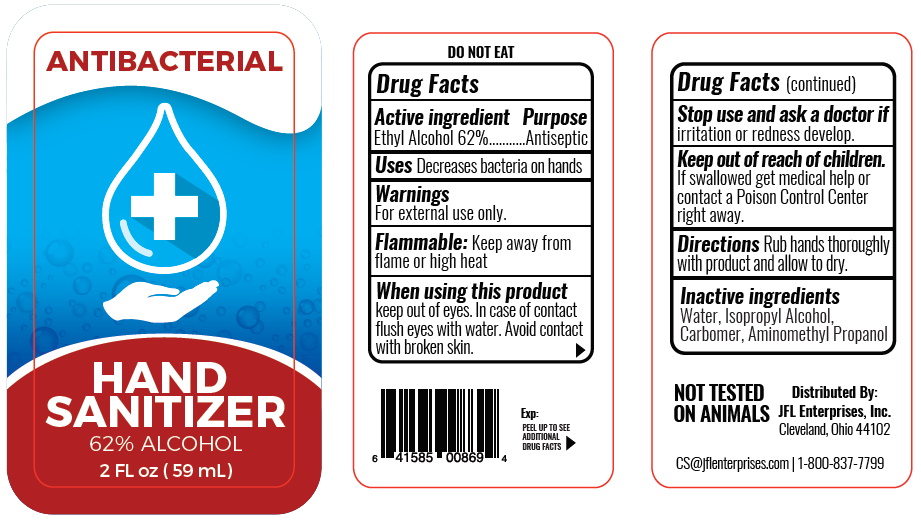 DRUG LABEL: Antibacterial Hand Sanitizer 
NDC: 71246-5030 | Form: GEL
Manufacturer: JFL ENTERPRISES, INC
Category: otc | Type: HUMAN OTC DRUG LABEL
Date: 20190101

ACTIVE INGREDIENTS: ALCOHOL 62 mL/100 mL
INACTIVE INGREDIENTS: AMINOMETHYL PROPANEDIOL; CARBOMER HOMOPOLYMER TYPE B (ALLYL SUCROSE CROSSLINKED); ISOPROPYL ALCOHOL; WATER

ANTIBACTERIAL HAND SANITIZER

Active ingredient Purpose

Ethyl Alcohol 62% ........................................Antiseptic

Purpose

Antiseptic Hand Sanitizer

Use

Decrease bacteria on hands

Warnings

External Use Only.

Flammable: Keep away from flame or high heat

Keep out of reach of children

if swallowed get medical help or contact a Poison Control Center right away.

Directions

Rub hands thoroughly with product and allow to dry.

Inactive Ingredient

Aminomethyl Propanol, Carbomer, Isopropyl Alcohol, Water

Stop and Ask a doctor if

Irritation or redness develop.

HOW SUPPLIED

Product: 71246-50309

NDC: 71246-5030-1 59 mL in a BOTTLE